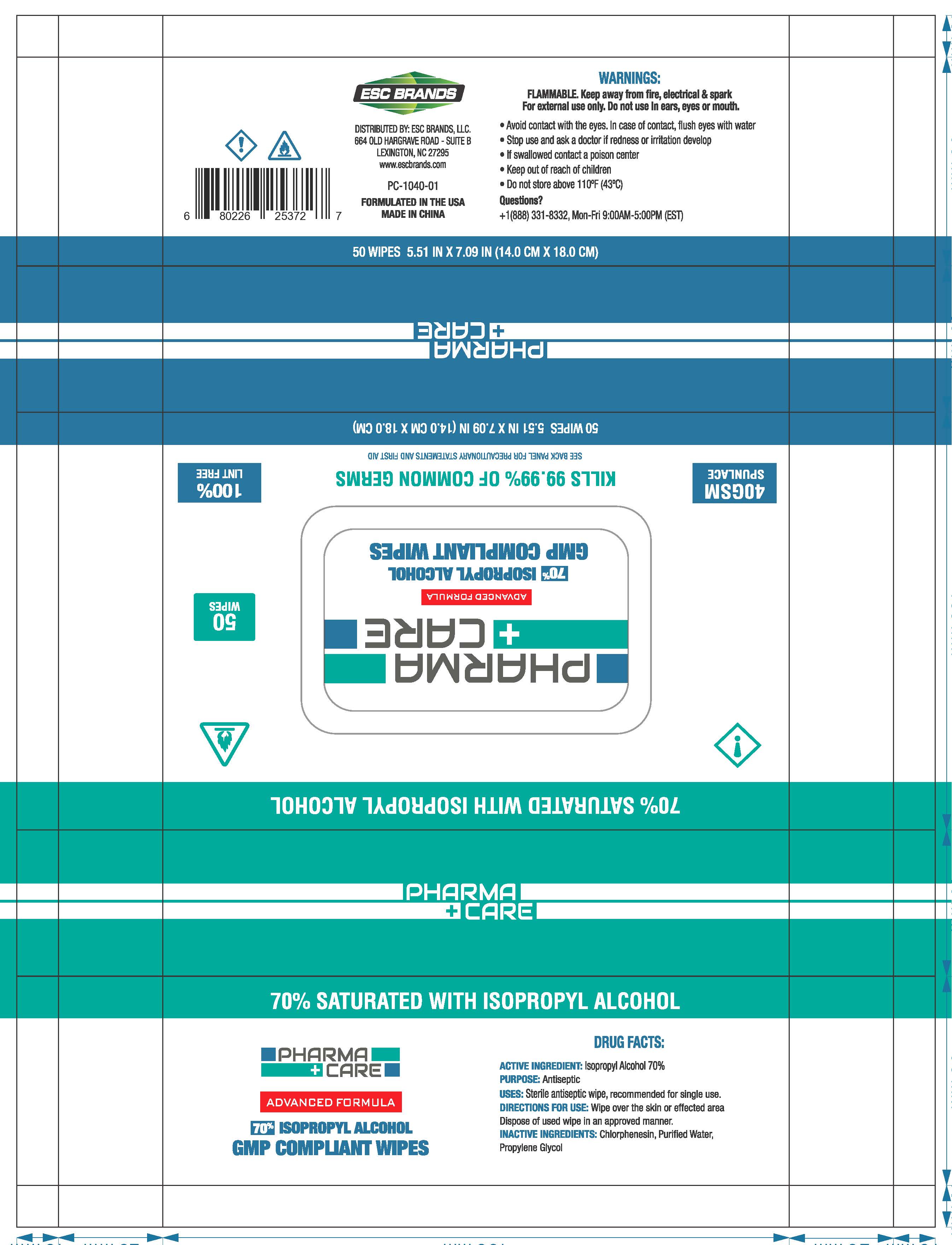 DRUG LABEL: Sanitizing  wipes
NDC: 51706-908 | Form: CLOTH
Manufacturer: Landy International
Category: otc | Type: HUMAN OTC DRUG LABEL
Date: 20200614

ACTIVE INGREDIENTS: ISOPROPYL ALCOHOL 70 g/100 g
INACTIVE INGREDIENTS: CHLORPHENESIN; PROPYLENE GLYCOL; WATER

51706-908 Sanitizing wipes Isopropyl Alcohol(70%active)

Active Ingredient(s)

ACTIVE INGREDIENT: Isopropyl Alcohol 70%

Purpose

Antiseptic

Use

USES: Sterile antiseptic wipe, recommended for single use.

Warnings

FLAMMABLE. Keep away from fire, electrical & spark
For external use only. Do not use In ears, eyes or mouth.
●Avoid contact with the eyes. In case of contact, flush eyes with water
●Stop use and ask a doctor if redness or iritation develop
●If swallowed contact a poison center

Keep out of reach of children.

Directions

USES: Sterile antiseptic wipe, recommended for single use.

Inactive ingredients

INACTIVE INGREDIENTS: Chlorphenesin, Purified Water,
Propylene Glycol